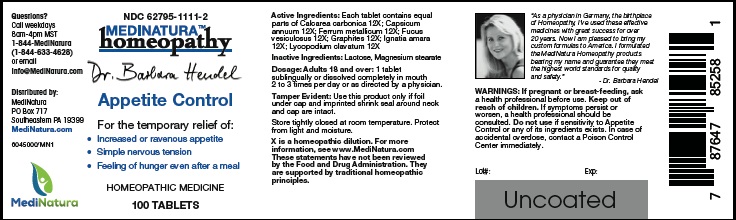 DRUG LABEL: Dr. Hendel Appetite Control
NDC: 62795-1111 | Form: TABLET
Manufacturer: MediNatura Inc
Category: homeopathic | Type: HUMAN OTC DRUG LABEL
Date: 20220817

ACTIVE INGREDIENTS: OYSTER SHELL CALCIUM CARBONATE, CRUDE 12 [hp_X]/1 1; CAPSICUM 12 [hp_X]/1 1; IRON 12 [hp_X]/1 1; FUCUS VESICULOSUS 12 [hp_X]/1 1; GRAPHITE 12 [hp_X]/1 1; STRYCHNOS IGNATII SEED 12 [hp_X]/1 1; LYCOPODIUM CLAVATUM SPORE 12 [hp_X]/1 1
INACTIVE INGREDIENTS: LACTOSE MONOHYDRATE; MAGNESIUM STEARATE

Dr. Hendel Appetite Control

WARNINGS

If pregnant or breast-feeding, ask a health professional before use. Keep out of reach of children. If symptoms persist or worsen, a health professional should be consulted. Do not use if sensitivity to Appetite Control or any of its ingredients exists. In case of accidental overdose, contact a Poison Control Center immediately.

KEEP OUT OF REACH OF CHILDREN

INDICATIONS

Appetite Control

INGREDIENTS

Each tablet contains equal parts of Calcarea carbonica 12X; Capsicum annuum 12X; Ferrum metallicum 12X; Fucus vesiculosus 12X; Graphites 12X; Ignatia amara 12X; Lycopodium clavatum 12X

INACTIVE INGREDIENT

Lactose, Magnesium stearate

DIRECTIONS

Adults 18 and over: 1 tablet sublingually or dissolved completely in mouth 2 to 3 times per day or as directed by a physician

USES

For the temporary relief of:

• Increased or ravenous appetite

• Simple nervous tension

• Feeling of hunger even after a meal

PACKAGE LABEL

Add image transcription here...